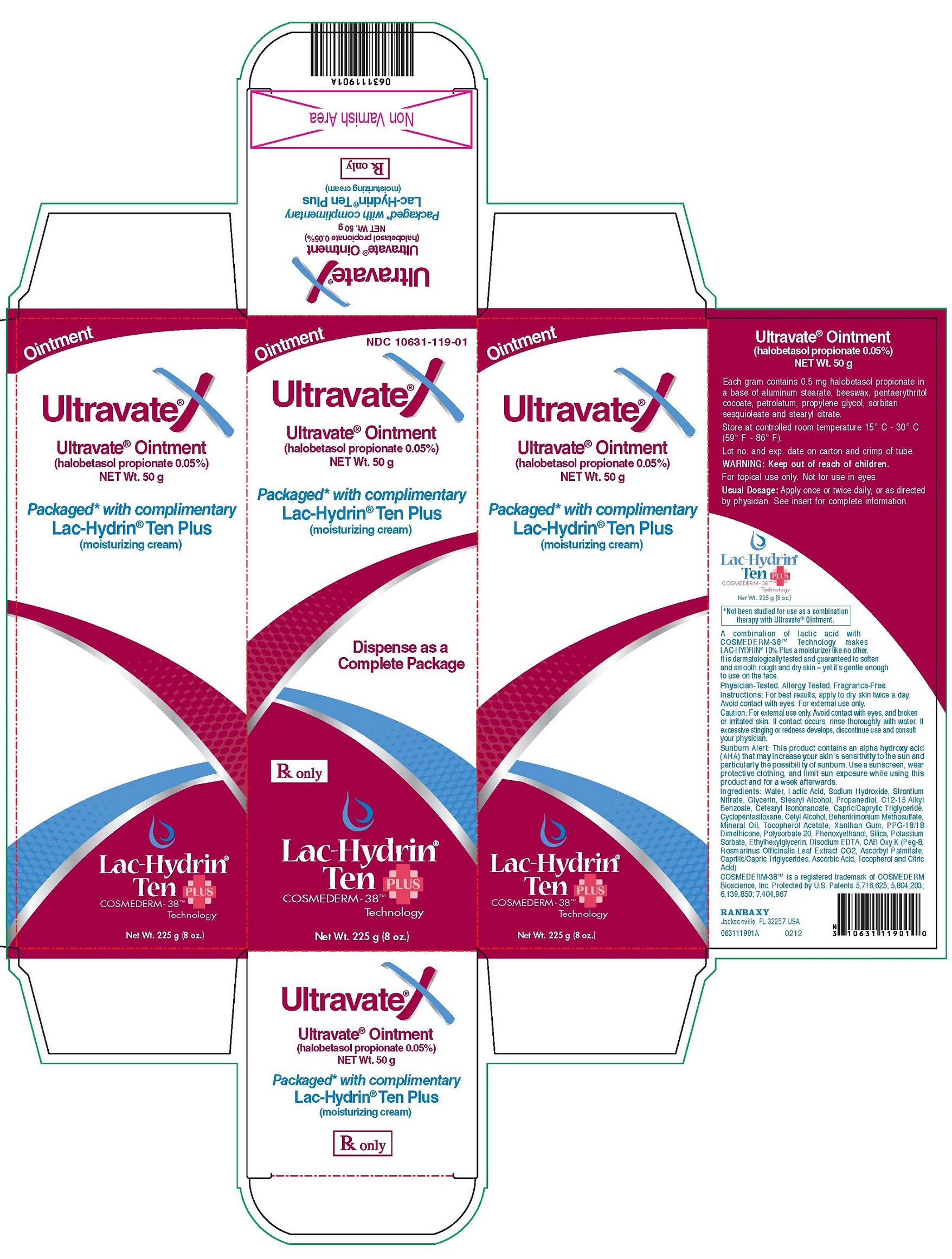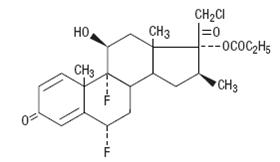 DRUG LABEL: Ultravate X
NDC: 10631-119 | Form: KIT | Route: TOPICAL
Manufacturer: Ranbaxy Laboratories Inc.
Category: prescription | Type: HUMAN PRESCRIPTION DRUG LABEL
Date: 20121108

ACTIVE INGREDIENTS: HALOBETASOL PROPIONATE 0.50 mg/1 g; AMMONIUM LACTATE 100 mg/1 g
INACTIVE INGREDIENTS: ALUMINUM STEARATE; YELLOW WAX; PETROLATUM; PROPYLENE GLYCOL; MONOSTEARYL CITRATE; SORBITAN SESQUIOLEATE; PENTAERYTHRITOL; ALKYL (C12-15) BENZOATE; ALPHA-TOCOPHEROL ACETATE; ASCORBIC ACID; ASCORBYL PALMITATE; BEHENTRIMONIUM METHOSULFATE; CETEARYL ISONONANOATE; CETYL ALCOHOL; CITRIC ACID MONOHYDRATE; CYCLOMETHICONE; EDETATE DISODIUM; ETHYLHEXYLGLYCERIN; GLYCERIN; LACTIC ACID; MINERAL OIL; PHENOXYETHANOL; POLYETHYLENE GLYCOL 400; POLYSORBATE 20; POTASSIUM SORBATE; PROPANEDIOL; ROSEMARY; SILICON DIOXIDE; SODIUM HYDROXIDE; STEARYL ALCOHOL; STRONTIUM NITRATE; TOCOPHEROL; TRICAPRYLIN; WATER; XANTHAN GUM

ULTRAVATE X
(halobetasol propionate ointment) Ointment, 0.05%
For Dermatological Use Only. Not for Ophthalmic Use.
Rx only

DESCRIPTION

Ultravate® (halobetasol propionate) ointment, 0.05% contains halobetasol propionate, a synthetic corticosteroid for topical dermatological use. The corticosteroids constitute a class of primarily synthetic steroids used topically as an anti-inflammatory and antipruritic agent.

Chemically halobetasol propionate is 21-chloro-6α, 9-difluoro-11β, 17-dihydroxy-16β-methylpregna-1, 4-diene-3-20-dione, 17-propionate, C25H31ClF2O5. It has the following structural formula:

Halobetasol propionate has the molecular weight of 485. It is a white crystalline powder insoluble in water.

Each gram of Ultravate Ointment contains 0.5 mg/g of halobetasol propionate in a base of aluminum stearate, beeswax, pentaerythritol cocoate, petrolatum, propylene glycol, sorbitan sesquioleate, and stearyl citrate.

CLINICAL PHARMACOLOGY

Like other topical corticosteroids, halobetasol propionate has anti-inflammatory, antipruritic and vasoconstrictive actions. The mechanism of the anti-inflammatory activity of the topical corticosteroids, in general, is unclear. However, corticosteroids are thought to act by the induction of phospholipase A2 inhibitory proteins, collectively called lipocortins. It is postulated that these proteins control the biosynthesis of potent mediators of inflammation such as prostaglandins and leukotrienes by inhibiting the release of their common precursor arachidonic acid. Arachidonic acid is released from membrane phospholipids by phospholipase A2.

Pharmacokinetics

The extent of percutaneous absorption of topical corticosteroids is determined by many factors including the vehicle and the integrity of the epidermal barrier. Occlusive dressings with hydrocortisone for up to 24 hours have not been demonstrated to increase penetration; however, occlusion of hydrocortisone for 96 hours markedly enhances penetration. Topical corticosteroids can be absorbed from normal intact skin. Inflammation and/or other disease processes in the skin may increase percutaneous absorption.

Human and animal studies indicate that less than 6% of the applied dose of halobetasol propionate enters the circulation within 96 hours following topical administration of the ointment.

Studies performed with Ultravate Ointment indicate that it is in the super-high range of potency as compared with other topical corticosteroids.

INDICATIONS AND USAGE

Ultravate Ointment 0.05% is a super-high potency corticosteroid indicated for the relief of the inflammatory and pruritic manifestations of corticosteroid-responsive dermatoses. Treatment beyond two consecutive weeks is not recommended, and the total dosage should not exceed 50 g/week because of the potential for the drug to suppress the hypothalamic-pituitary-adrenal (HPA) axis. Use in children under 12 years of age is not recommended.

As with other highly active corticosteroids, therapy should be discontinued when control has been achieved. If no improvement is seen within 2 weeks, reassessment of the diagnosis may be necessary.

CONTRAINDICATIONS

Ultravate Ointment is contraindicated in those patients with a history of hypersensitivity to any of the components of the preparation.

PRECAUTIONS

General

Systemic absorption of topical corticosteroids can produce reversible hypothalamic-pituitary-adrenal (HPA) axis suppression with the potential for glucocorticosteroid insufficiency after withdrawal of treatment. Manifestations of Cushing’s syndrome, hyperglycemia, and glucosuria can also be produced in some patients by systemic absorption of topical corticosteroids while on treatment.

Patients applying a topical steroid to a large surface area or to areas under occlusion should be evaluated periodically for evidence of HPA axis suppression. This may be done by using the ACTH stimulation, A.M. plasma cortisol, and urinary free-cortisol tests. Patients receiving super potent corticosteroids should not be treated for more than 2 weeks at a time and only small areas should be treated at any one time due to the increased risk of HPA suppression.

Ultravate Ointment produced HPA axis suppression when used in divided doses at 7 grams per day for one week in patients with psoriasis. These effects were reversible upon discontinuation of treatment.

If HPA axis suppression is noted, an attempt should be made to withdraw the drug, to reduce the frequency of application, or to substitute a less potent corticosteroid. Recovery of HPA axis function is generally prompt upon discontinuation of topical corticosteroids. Infrequently, signs and symptoms of glucocorticosteroid insufficiency may occur requiring supplemental systemic corticosteroids. For information on systemic supplementation, see prescribing information for those products.

Pediatric patients may be more susceptible to systemic toxicity from equivalent doses due to their larger skin surface to body mass ratios (see PRECAUTIONS: Pediatric Use).

If irritation develops, Ultravate Ointment should be discontinued and appropriate therapy instituted. Allergic contact dermatitis with corticosteroids is usually diagnosed by observing failure to heal rather than noting a clinical exacerbation as with most topical products not containing corticosteroids. Such an observation should be corroborated with appropriate diagnostic patch testing.

If concomitant skin infections are present or develop, an appropriate antifungal or antibacterial agent should be used. If a favorable response does not occur promptly, use of Ultravate Ointment should be discontinued until the infection has been adequately controlled.

Ultravate Ointment should not be used in the treatment of rosacea or perioral dermatitis, and it should not be used on the face, groin, or in the axillae.

Information for Patients

Patients using Ultravate® Ointment should receive the following information and instructions:

1. The medication is to be used as directed by the physician. It is for external use only. Avoid contact with the eyes.
2. The medication should not be used for any disorder other than that for which it was prescribed.
3. The treated skin area should not be bandaged, otherwise covered or wrapped, so as to be occlusive unless directed by the physician.
4. Patients should report to their physician any signs of local adverse reactions.

Laboratory Tests

The following tests may be helpful in evaluating patients for HPA axis suppression: ACTH-stimulation test; A.M. plasma cortisol test; Urinary free-cortisol test.

Carcinogenesis, Mutagenesis, and Impairment of Fertility

Long-term animal studies have not been performed to evaluate the carcinogenic potential of halobetasol propionate. Positive mutagenicity effects were observed in two genotoxicity assays. Halobetasol propionate was positive in a Chinese hamster micronucleus test, and in a mouse lymphoma gene mutation assay in vitro.

Studies in the rat following oral administration at dose levels up to 50 mcg/kg/day indicated no impairment of fertility or general reproductive performance.

In other genotoxicity testing, halobetasol propionate was not found to be genotoxic in the Ames/Salmonella assay, in the sister chromatid exchange test in somatic cells of the Chinese hamster, in chromosome aberration studies of germinal and somatic cells of rodents, and in a mammalian spot test to determine point mutations.

Pregnancy

Teratogenic effects: Pregnancy Category C

Corticosteroids have been shown to be teratogenic in laboratory animals when administered systemically at relatively low dosage levels. Some corticosteroids have been shown to be teratogenic after dermal application in laboratory animals.

Halobetasol propionate has been shown to be teratogenic in SPF rats and chinchilla-type rabbits when given systemically during gestation at doses of 0.04 to 0.1 mg/kg in rats and 0.01 mg/kg in rabbits. These doses are approximately 13, 33 and 3 times, respectively, the human topical dose of Ultravate Ointment. Halobetasol propionate was embryotoxic in rabbits but not in rats.

Cleft palate was observed in both rats and rabbits. Omphalocele was seen in rats, but not in rabbits.

There are no adequate and well-controlled studies of the teratogenic potential of halobetasol propionate in pregnant women. Ultravate Ointment should be used during pregnancy only if the potential benefit justifies the potential risk to the fetus.

Nursing Mothers

Systemically administered corticosteroids appear in human milk and could suppress growth, interfere with endogenous corticosteroid production, or cause other untoward effects. It is not known whether topical administration of corticosteroids could result in sufficient systemic absorption to produce detectable quantities in human milk. Because many drugs are excreted in human milk, caution should be exercised when Ultravate Ointment is administered to a nursing woman.

Pediatric Use

Safety and effectiveness of Ultravate Ointment in pediatric patients have not been established and use in pediatric patients under 12 is not recommended. Because of a higher ratio of skin surface area to body mass, pediatric patients are at a greater risk than adults of HPA axis suppression and Cushing’s syndrome when they are treated with topical corticosteroids. They are therefore also at greater risk of adrenal insufficiency during or after withdrawal of treatment. Adverse effects including striae have been reported with inappropriate use of topical corticosteroids in infants and children.

HPA axis suppression, Cushing’s syndrome, linear growth retardation, delayed weight gain and intracranial hypertension have been reported in children receiving topical corticosteroids. Manifestations of adrenal suppression in children include low plasma cortisol levels and an absence of response to ACTH stimulation. Manifestations of intracranial hypertension include bulging fontanelles, headaches, and bilateral papilledema.

Geriatric Use

Of approximately 400 patients treated with Ultravate® Ointment in clinical studies, 25% were 61 years and over and 6% were 71 years and over. No overall differences in safety or effectiveness were observed between these patients and younger patients; and other reported clinical experience has not identified differences in responses between the elderly and younger patients, but greater sensitivity of some older individuals cannot be ruled out.

ADVERSE REACTIONS

In controlled clinical trials, the most frequent adverse events reported for Ultravate Ointment included stinging or burning in 1.6% of the patients. Less frequently reported adverse reactions were pustulation, erythema, skin atrophy, leukoderma, acne, itching, secondary infection, telangiectasia, urticaria, dry skin, miliaria, paresthesia, and rash.

The following additional local adverse reactions are reported infrequently with topical corticosteroids, and they may occur more frequently with high potency corticosteroids, such as Ultravate Ointment. These reactions are listed in an approximate decreasing order of occurrence: folliculitis, hypertrichosis, acneiform eruptions, hypopigmentation, perioral dermatitis, allergic contact dermatitis, secondary infection, striae and miliaria.

OVERDOSAGE

Topically applied Ultravate Ointment can be absorbed in sufficient amounts to produce systemic effects (see PRECAUTIONS).

DOSAGE AND ADMINISTRATION

Apply a thin layer of Ultravate Ointment to the affected skin once or twice daily, as directed by your physician, and rub in gently and completely.

Ultravate (halobetasol propionate) Ointment is a super-high potency topical corticosteroid; therefore, treatment should be limited to two weeks, and amounts greater than 50 g/wk should not be used. As with other corticosteroids, therapy should be discontinued when control is achieved. If no improvement is seen within 2 weeks, reassessment of diagnosis may be necessary.

Ultravate Ointment should not be used with occlusive dressings.

HOW SUPPLIED

Ultravate® (halobetasol propionate) Ointment, 0.05% is supplied in the following tube size:

50 g (NDC 10631-102-50)

STORAGE

Store between 15°C and 30°C (59°F and 86°F).

To report SUSPECTED ADVERSE REACTIONS, contact the FDA at 1-800-FDA-1088 or www.fda.gov/medwatch.

5090133 (Flat), 5090134 (Folded)

Revised November 2011